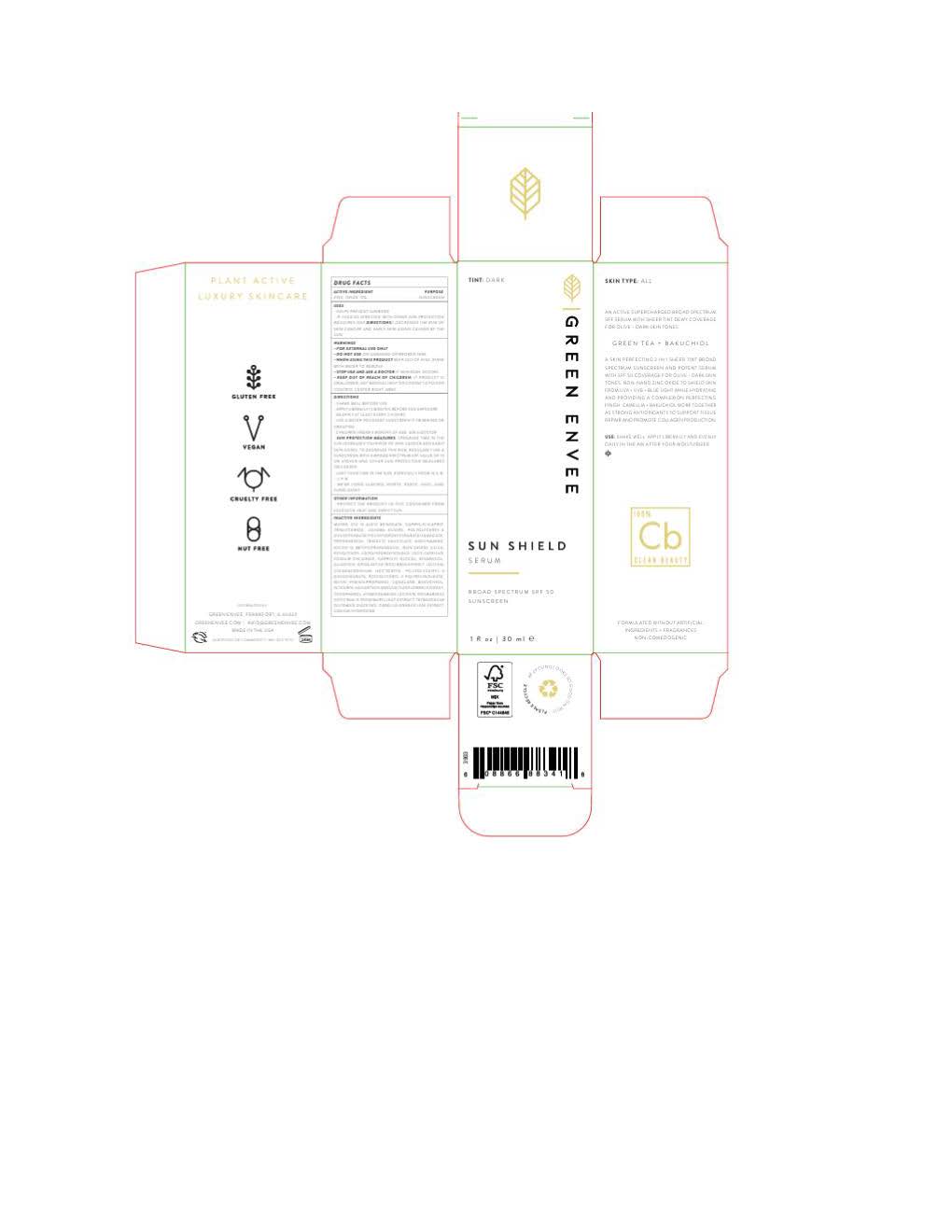 DRUG LABEL: Green Envee Sun Shield Serum
NDC: 83678-2049 | Form: LOTION
Manufacturer: Green Envee
Category: otc | Type: HUMAN OTC DRUG LABEL
Date: 20251017

ACTIVE INGREDIENTS: ZINC OXIDE 132 mg/1 mL
INACTIVE INGREDIENTS: TETRASODIUM GLUTAMATE DIACETATE; SODIUM CHLORIDE; POLYGLYCERYL-4 DIISOSTEARATE/POLYHYDROXYSTEARATE/SEBACATE; CAPRYLIC/CAPRIC TRIGLYCERIDE; TRIDECYL SALICYLATE; ORYZA SATIVA WHOLE; WATER; NIACINAMIDE; NYLON-12; COCO-CAPRYLATE; HYDROLYZED JOJOBA ESTERS; .ALPHA.-BISABOLOL, (+)-; PROPANEDIOL; LECITHIN, SOYBEAN; ALLANTOIN; SILICON DIOXIDE; TOCOPHEROL; CAPRYLYL GLYCOL; PHENYLPROPANOL; HELIANTHUS ANNUUS FLOWERING TOP; METHYLPROPANEDIOL; POLYGLYCERYL-2 DIPOLYHYDROXYSTEARATE; POLYGLYCERYL-3 DIISOSTEARATE; GLYCERIN; STEARALKONIUM HECTORITE; FERRIC OXIDE RED; FERRIC OXIDE YELLOW; FERROSOFERRIC OXIDE; RUTIN; CAMELLIA SINENSIS LEAF OIL; SQUALANE; BAKUCHIOL; SODIUM HYDROXIDE; ALKYL (C12-15) BENZOATE; ROSMARINUS OFFICINALIS FLOWER

Green Envee Sun Shield Serum